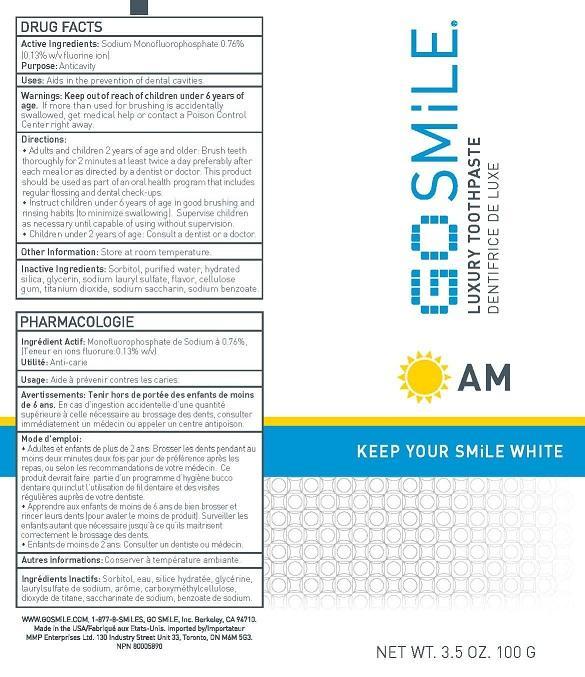 DRUG LABEL: GO SMILE LUXURY
NDC: 44873-106 | Form: PASTE, DENTIFRICE
Manufacturer: Go Smile, Inc.
Category: otc | Type: HUMAN OTC DRUG LABEL
Date: 20231115

ACTIVE INGREDIENTS: SODIUM MONOFLUOROPHOSPHATE 0.13 g/100 g
INACTIVE INGREDIENTS: SORBITOL; WATER; HYDRATED SILICA; GLYCERIN; SODIUM LAURYL SULFATE; CARBOXYMETHYLCELLULOSE; TITANIUM DIOXIDE; SODIUM BENZOATE; SACCHARIN SODIUM

GOSMILE (as PLD) - LUXURY TOOTHPASTE, AM (44873-106)

ACTIVE INGREDIENTS

SODIUM MONOFLUOROPHOSPHATE 0.76% (0.13% w/v FLUORIDE ION)

PURPOSE

ANTICAVITY

USES

AIDS IN THE PREVENTION OF DENTAL CAVITIES.

WARNINGS

KEEP OUT OF REACH OF CHILDREN UNDER 6 YEARS OLD.

DIRECTIONS

- ADULTS AND CHILDREN 2 YEARS OF AGE AND OLDER: BRUSH TEETH THOROUGHLY FOR TWO MINUTES AT LEAST TWICE A DAY PREFERABLY AFTER EACH MEAL OR AS DIRECTED BY A DOCTOR OR DENTIST. THIS PRODUCT SHOULD BE USED AS PART OF AN ORAL HEALTH PROGRAM THAT INCLUDES REGULAR FLOSSING AND DENTAL CHECK-UPS.
- INSTRUCT CHILDREN UNDER 6 YEARS OF AGE IN GOOD BRUSHING AND RINSING HABITS (TO MINIMIZE SWALLOWING). SUPERVISE CHILDREN AS NECESSARY UNTIL CAPABLE OF USING WITHOUT SUPERVISION.
- CHILDREN UNDER TWO YEARS OF AGE: CONSULT A DENTIST OR A DOCTOR.

INACTIVE INGREDIENTS

SORBITOL, PURIFIED WATER, HYDRATED SILICA, GLYCERIN, SODIUM LAURYL SULFATE, FLAVOR, CELLULOSE GUM, TITANIUM DIOXIDE, SODIUM SACCHARIN, SODIUM BENZOATE.

OTHER INFORMATION

STORE AT ROOM TEMPERATURE.

WARNINGS

IF MORE THAN USED FOR BRUSHING IS ACCIDENTALLY SWALLOWED, GET MEDICAL HELP OR CONTACT A POISON CONTROL CENTER RIGHT AWAY.